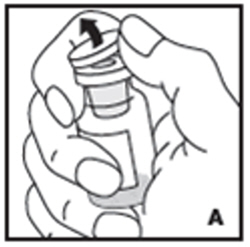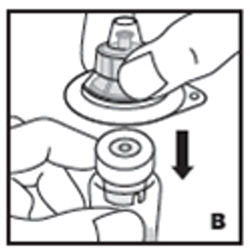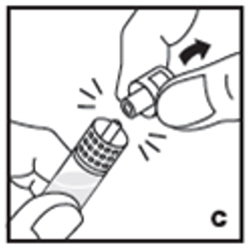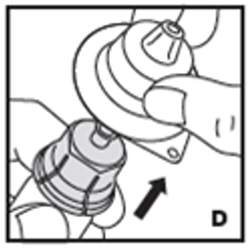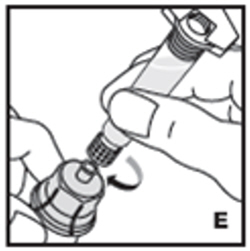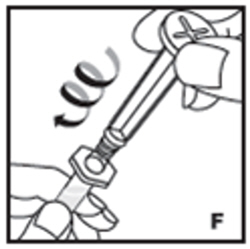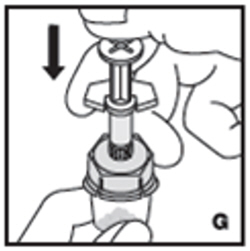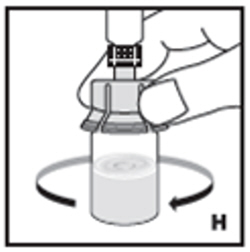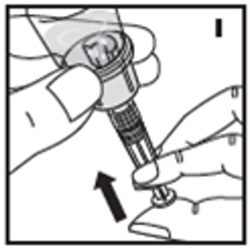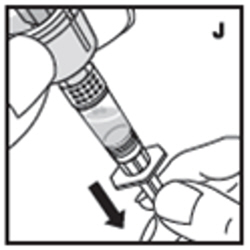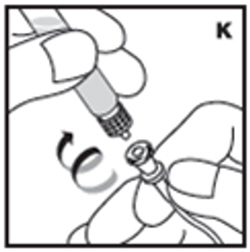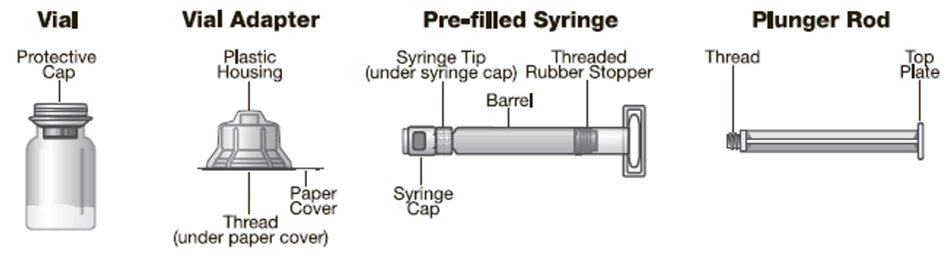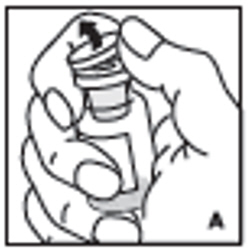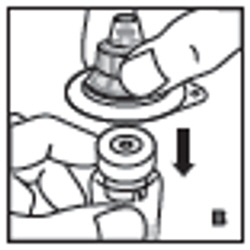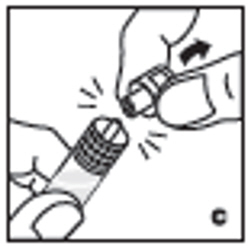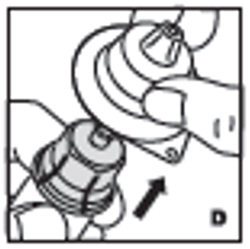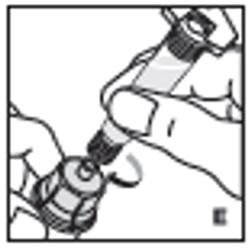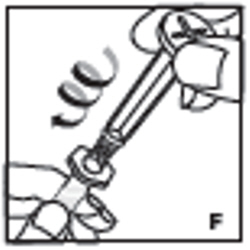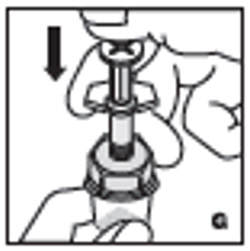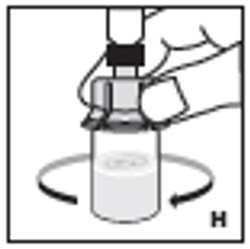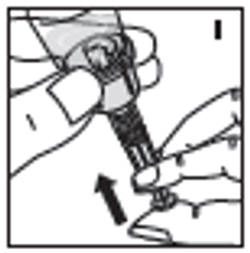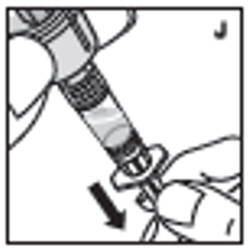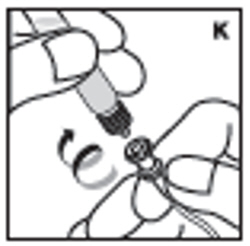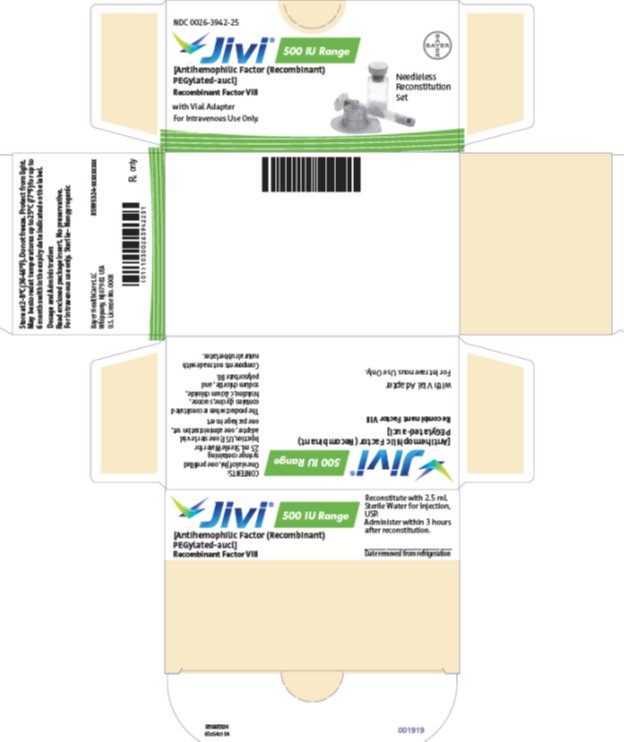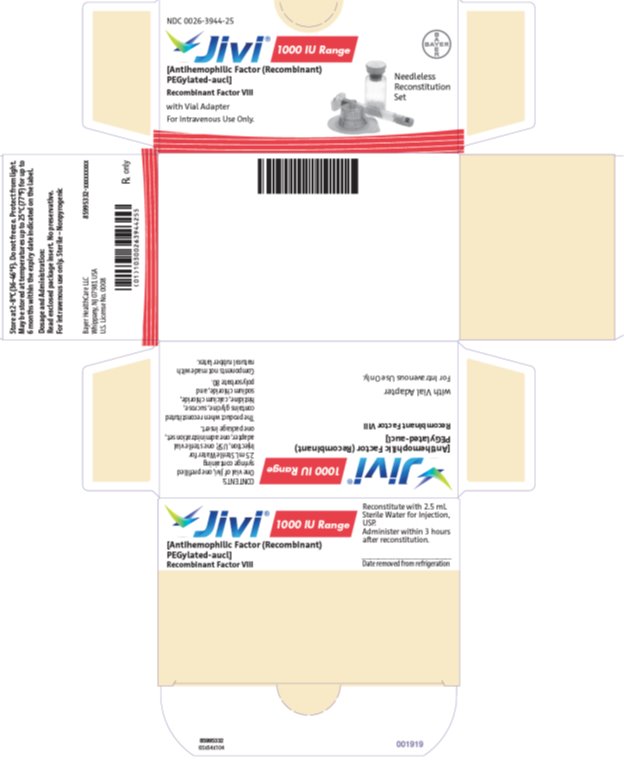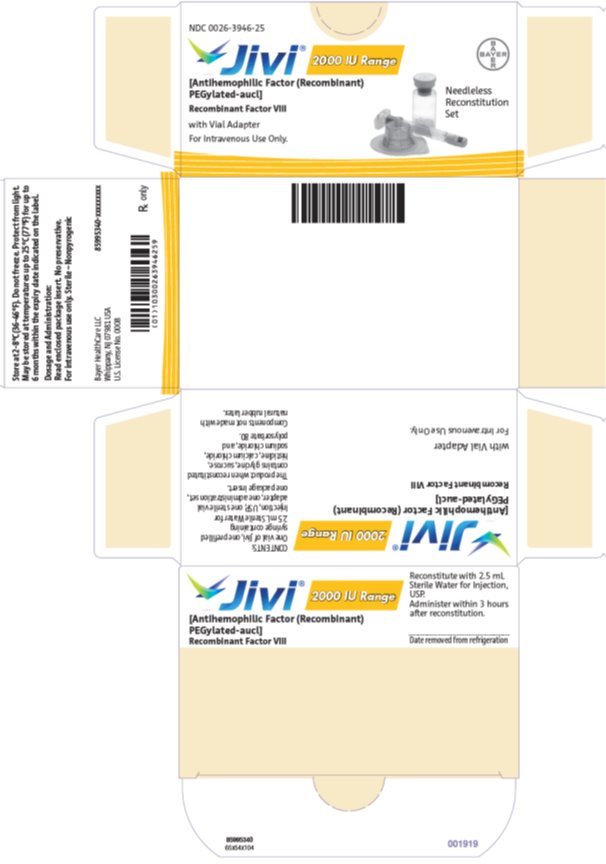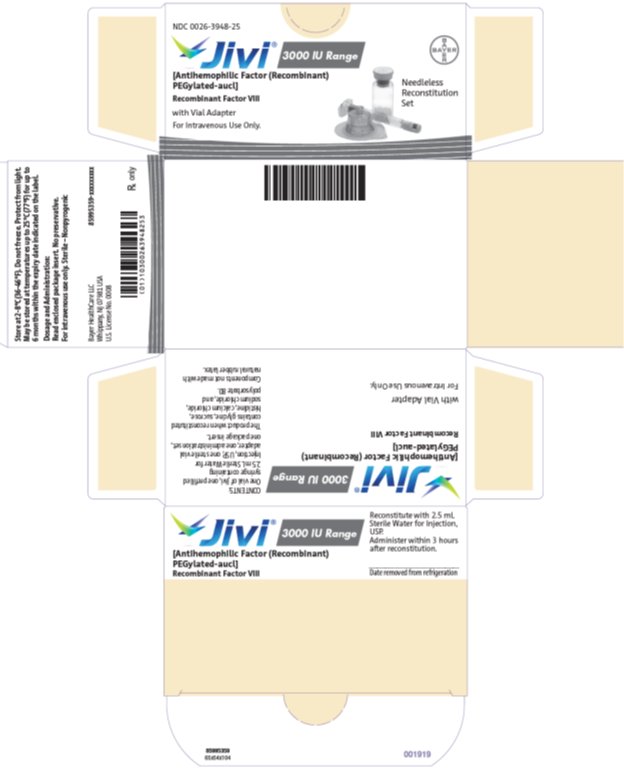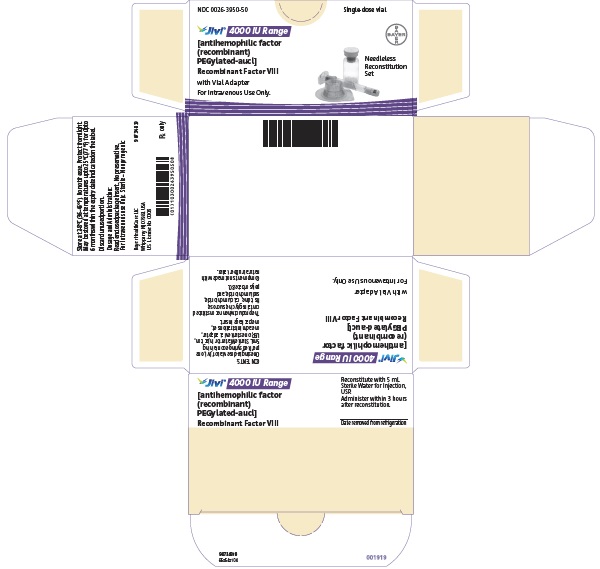 DRUG LABEL: Jivi
NDC: 0026-3942 | Form: KIT | Route: INTRAVENOUS
Manufacturer: Bayer HealthCare LLC
Category: other | Type: PLASMA DERIVATIVE
Date: 20250527

ACTIVE INGREDIENTS: DAMOCTOCOG ALFA PEGOL 500 [iU]/2.5 mL
INACTIVE INGREDIENTS: CALCIUM CHLORIDE; GLYCINE; HISTIDINE; POLYSORBATE 80; SUCROSE; SODIUM CHLORIDE; WATER

HIGHLIGHTS OF PRESCRIBING INFORMATION

These highlights do not include all the information needed to use JIVI safely and effectively. See full prescribing information for JIVI.
JIVI® [antihemophilic factor (recombinant), PEGylated-aucl] lyophilized powder for solution, for intravenous use
Initial U.S. Approval: 2018

RECENT MAJOR CHANGES

Indications and Usage (1) | 5/2025
Dosage and Administration (2.1) | 5/2025
Warnings and Precautions (5.3) | 5/2025

1 INDICATIONS AND USAGE

JIVI, is a recombinant DNA-derived, Factor VIII concentrate indicated for use in previously treated adults and pediatric patients 7 years of age and older with hemophilia A (congenital Factor VIII deficiency) for:

- On-demand treatment and control of bleeding episodes
- Perioperative management of bleeding
- Routine prophylaxis to reduce the frequency of bleeding episodes (1)

Limitations of use

JIVI is not indicated for use in:

- Children < 7 years of age due to a greater risk for hypersensitivity reactions and/or loss of efficacy. (1, 8.4)
- Previously untreated patients (PUPs). (1)
- Treatment of von Willebrand disease. (1)

2 DOSAGE AND ADMINISTRATION

For intravenous use after reconstitution only.

Control of bleeding episodes and perioperative management

- Expected recovery: one unit per kilogram body weight of JIVI will increase the Factor VIII level by 2 international units per deciliter (IU/dL). Each vial of JIVI contains the labeled amount of recombinant Factor VIII in IU. (2.1)
- Required dose (IU) = body weight (kg) × desired Factor VIII rise (% of normal or IU/dL) × reciprocal of expected recovery (or observed recovery, if available). (2.1)
- Estimated Increment of Factor VIII (IU/dL or % of normal) = [Total Dose (IU)/body weight (kg)] × 2 (IU/dL per IU/kg). (2.1)

Routine prophylaxis

Adults and Adolescents (12 years of age and older):

- The recommended initial dosage regimen is 30–40 IU/kg twice weekly. (2.1)
- Based on the bleeding episodes:
  - The regimen may be adjusted to 45–60 IU/kg every 5 days.
  - A regimen may be further individually adjusted to less or more frequent dosing. (2.1)

Children (7 to <12 years of age):

- The recommended initial dosage regimen is 60 IU/kg twice weekly.
- Adjust the dose based on the patient's clinical response and/or recovery. (2.1, 5.3)

3 DOSAGE FORMS AND STRENGTHS

JIVI is available as lyophilized powder in single-dose vials containing nominally 500, 1000, 2000, 3000, or 4000 IU. (3)

4 CONTRAINDICATIONS

Do not use in patients who have a history of hypersensitivity reactions to the active substance, polyethylene glycol (PEG), mouse or hamster proteins, or other constituents of the product. (4)

5 WARNINGS AND PRECAUTIONS

- Hypersensitivity reactions, including severe allergic reactions, have occurred. Monitor patients for hypersensitivity symptoms. Should hypersensitivity symptoms occur, discontinue treatment with JIVI and administer appropriate treatment. Hypersensitivity reactions may also be related to antibodies against polyethylene glycol (PEG). (5.1, 5.3)
- Development of Factor VIII neutralizing antibodies have occurred. If expected plasma Factor VIII activity levels are not attained, or if bleeding is not controlled as expected with the administered dose, then perform an assay that measures Factor VIII inhibitor concentration. (5.2, 5.3)
- Immune response to PEG, manifested as symptoms of acute hypersensitivity and/or loss of drug effect, has occurred following JIVI administration. Discontinue JIVI and switch patients to a different anti-hemophilic product. (5.3, 6.1)

6 ADVERSE REACTIONS

The most common adverse reactions (incidence ≥ 5%) were headache, fever, cough, and abdominal pain. (6)

To report SUSPECTED ADVERSE REACTIONS, contact Bayer at 1-888-842-2937 or FDA at 1-800-FDA-1088 or www.fda.gov/medwatch.

8 USE IN SPECIFIC POPULATIONS

Pediatric Use: Higher clearance, a shorter half-life and lower incremental recovery of Factor VIII has been observed in children <12 years of age. (8.4)

FULL PRESCRIBING INFORMATION

1 INDICATIONS AND USAGE

JIVI, is indicated for use in previously treated adults and pediatric patients 7 years of age and older with hemophilia A (congenital Factor VIII deficiency) for:

- On-demand treatment and control of bleeding episodes
- Perioperative management of bleeding
- Routine prophylaxis to reduce the frequency of bleeding episodes

Limitations of Use

JIVI is not indicated for use in:

- Children < 7 years of age due to greater risk for hypersensitivity reactions and/or loss of efficacy [see Use in Specific Populations (8.4)]
- Previously untreated patients (PUPs)
- Treatment of von Willebrand disease

2 DOSAGE AND ADMINISTRATION

For intravenous use after reconstitution only.

2.1 Recommended Dosage

- Each vial label of JIVI states the Factor VIII potency in international units (IU). One IU is defined by the current WHO (World Health Organization) international standard for Factor VIII concentrate.
- Dosage and duration of treatment depend on the severity of the Factor VIII deficiency, the location and extent of bleeding, and the patient's clinical condition. Careful control of replacement therapy is especially important in cases of major surgery or life-threatening bleeding episodes.
- Potency assignment for JIVI is determined using a chromogenic substrate assay.
- Monitor the Factor VIII activity of JIVI in plasma using either a validated chromogenic substrate assay or a validated one-stage clotting assay [see Warnings and Precautions (5.4)].
- Calculation of the required dose of Factor VIII is based on the empirical finding that 1 IU of Factor VIII per kilogram body weight increases the plasma Factor VIII level by 2 IU/dL.
- Estimate the required dose for on-demand treatment and control of bleeding and perioperative management using the following formula:
  Required dose (IU) = body weight (kg) × desired Factor VIII rise (% of normal or IU/dL) × reciprocal of expected recovery (or observed recovery, if available) (e.g., 0.5 for a recovery of 2 IU/dL per IU/kg)
  Estimate the expected in vivo peak increase using the following formula:
  Estimated increment of Factor VIII (IU/dL or % of normal) = [Total dose (IU)/body weight (kg)] × 2 (IU/dL per IU/kg)
- Adjust dose and frequency to the patient's clinical response. Patients may vary in their pharmacokinetic [e.g., half-life, incremental recovery and AUC (area under the curve)] and clinical responses to JIVI.
- The total recommended maximum dose per infusion is approximately 6000 IU (rounded to vial size) [see Clinical Studies (14)].

On-demand Treatment and Control of Bleeding Episodes

A guide for dosing JIVI for the on-demand treatment and control of bleeding episodes is provided in Table 1. The goal of treatment is to maintain a plasma Factor VIII activity level at or above the plasma levels (in % of normal or in IU/dL) outlined in Table 1.

Table 1: Dosing for Control of Bleeding Episodes
Degree of Bleeding Hemorrhage/Hemorrhagic Event | Factor VIII Level Required (IU/dL or % of normal) | Dose (IU/kg) | Frequency of Doses (hours) | Duration of Treatment
Minor (e.g., early hemarthrosis, minor muscle bleeding, oral bleeds) | 20–40 | 10–20 | Repeat every 24–48 hours | Until bleeding is resolved
Moderate (e.g., more extensive hemarthrosis, muscle bleeding, or hematoma) | 30–60 | 15–30 | Repeat every 24–48 hours | Until bleeding is resolved
Major (e.g., intracranial, intra-abdominal or intrathoracic hemorrhages, gastrointestinal bleeding, central nervous system bleeding, bleeding in the retropharyngeal or retroperitoneal spaces, or iliopsoas sheath, life- or limb- threatening hemorrhage) | 60–100 | 30–50 | Repeat every 8–24 hours | Until bleeding is resolved

Perioperative Management of Bleeding

A guide for dosing JIVI during surgery (perioperative management) is provided in Table 2. The goal of treatment is to maintain a plasma Factor VIII activity level at or above the plasma level (in % of normal or in IU/dL) outlined in Table 2. During major surgery, monitoring with appropriate laboratory tests, including serial Factor VIII activity assays, is highly recommended [see Warnings and Precautions (5.4)].

Table 2: Dosing for Perioperative Management
Type of Surgery | Factor VIII Level Required (IU/dL or % of normal) | Dose (IU/kg) | Frequency of Doses (hours) | Duration of Treatment (days)
Minor (e.g., tooth extraction) | 30–60 (pre- and post-operative) | 15–30 | Repeat every 24 hours | At least 1 day until healing is achieved
Major (e.g., intracranial, intra-abdominal, intrathoracic, or joint replacement surgery) | 80–100 (pre- and post-operative) | 40–50 | Repeat every 12–24 hours | Until adequate wound healing is complete, then continue therapy for at least another 7 days to maintain Factor VIII activity of 30–60% (IU/dL)

Routine Prophylaxis

Adults and Adolescents (12 years of age and older):

- The recommended initial dosage regimen is 30–40 IU/kg twice weekly.
- Based on the bleeding episodes:
  - The regimen may be adjusted to 45–60 IU/kg every 5 days.
  - A regimen may be further individually adjusted to less or more frequent dosing.

Children (7 to <12 years of age):

- The recommended initial dosage regimen is 60 IU/kg twice weekly.
- Adjust the dose based on the patient's clinical response and/or recovery [see Warnings and Precautions (5.3)].

2.2 Preparation and Reconstitution

Reconstitute and administer JIVI with the components provided with each package. If any component of the package is opened or damaged, do not use this component.

Reconstitution

Work on a clean surface and wash hands thoroughly using soap and warm water before performing the procedures.

1. Warm both unopened JIVI vial and prefilled diluent syringe in your hands to a comfortable temperature (do not exceed 37°C or 99°F).

2. Remove the protective cap from the vial (A). Aseptically cleanse the rubber stopper with a sterile alcohol swab, being careful not to handle the rubber stopper.

3. Place the product vial on a firm, non-skid surface. Peel off the paper cover on the vial adapter plastic housing. Do not remove the adapter from the plastic housing. Holding the adapter housing, place over the product vial and firmly press down (B). The adapter will snap over the vial cap. Do not remove the adapter housing at this step.

4. Holding the syringe by the barrel, snap the syringe cap off the tip (C). Do not touch the syringe tip with your hand or any surface. Set the syringe aside for further use.

5. Now remove and discard the adapter plastic housing (D).

6. Attach the prefilled syringe to the vial adapter thread by turning clockwise (E).

7. Remove the clear plastic plunger rod from the carton. Grasp the plunger rod by the top plate. Avoid touching the sides and threads of the plunger rod. Attach the plunger rod by turning it clockwise into the threaded rubber stopper of the prefilled syringe (F).

8. Inject the diluent slowly by pushing down on the plunger rod (G).

9. Swirl vial gently until all powder on all sides of the vial is dissolved (H). Do not shake vial. Be sure that all powder is completely dissolved. Do not use if solution contains visible particles or is cloudy.

10. Push down on the plunger to push all air back into the vial. Then while holding the plunger down, turn the vial with syringe upside-down (invert) so the vial is now above the syringe (I). Pooling: If the dose requires more than one vial, reconstitute each vial as described above with the diluent syringe provided. Use a larger plastic syringe (not provided) to combine the contents of the vials into the syringe.

11. Filter the reconstituted product to remove potential particulate matter in the solution. Filtering is achieved by using the vial adapter. Withdraw all the solution through the vial adapter into the syringe by pulling the plunger rod back slowly and smoothly (J). Tilt the vial to the side and back to make sure all the solution has been drawn toward the large opening in the rubber stopper and into the syringe. Remove as much air as possible before removing the syringe from the vial by slowly and carefully pushing the air back into the vial.

12. Detach the syringe with plunger rod from the vial adapter by turning counter-clockwise. Attach the syringe to the infusion set provided and inject the reconstituted product intravenously (K).
  Note: follow instructions for infusion set provided.

2.3 Administration

For intravenous use only.

- Parenteral drug products should be inspected visually for particulate matter and discoloration prior to administration whenever solution and container permit.
- Do not use if you notice any particulate matter or discoloration and immediately contact Bayer Medical Communications at 1-888-84-BAYER (1-888-842-2937).
- Administer reconstituted JIVI as soon as possible. If not, store at room temperature for no longer than 3 hours.
- Infuse JIVI intravenously over a period of 1 to 15 minutes. Adapt the rate of administration to the response of each individual patient (maximum infusion rate 2.5 mL/min).

3 DOSAGE FORMS AND STRENGTHS

JIVI is available as a white to slightly yellow lyophilized powder in single-dose glass vials containing nominally 500, 1000, 2000, 3000, or 4000 IU of Factor VIII potency per vial.

Each vial of JIVI is labeled with actual Factor VIII potency expressed in IU determined using a chromogenic substrate assay. This potency assignment employs a Factor VIII concentrate standard that is referenced to the current WHO International Standard for Factor VIII concentrate, and is evaluated by appropriate methodology to ensure accuracy of the results.

4 CONTRAINDICATIONS

JIVI is contraindicated in patients who have a history of hypersensitivity reactions to the active substance, polyethylene glycol (PEG), mouse or hamster proteins, or other constituents of the product [see Description (11)].

5 WARNINGS AND PRECAUTIONS

5.1 Hypersensitivity Reactions

Hypersensitivity reactions, including severe allergic reactions, have occurred with JIVI. Monitor patients for hypersensitivity symptoms. Early signs of hypersensitivity reactions, which can progress to anaphylaxis, may include chest or throat tightness, dizziness, mild hypotension and nausea. If hypersensitivity reactions occur, immediately discontinue administration and initiate appropriate treatment.

JIVI may contain trace amounts of mouse and hamster proteins [see Description (11)]. Patients treated with this product may develop hypersensitivity to these non-human mammalian proteins.

Hypersensitivity reactions may also be related to antibodies against polyethylene glycol (PEG) [see Warnings and Precautions (5.3)].

5.2 Neutralizing Antibody Formation

Neutralizing antibody (inhibitor) formation have occurred following administration of JIVI. Carefully monitor patients for the development of Factor VIII inhibitors, using appropriate clinical observations and laboratory tests. If expected plasma Factor VIII activity levels are not attained or if bleeding is not controlled as expected with administered dose, suspect the presence of an inhibitor (neutralizing antibody) [see Warnings and Precautions (5.4)].

5.3 Immune Response to Polyethylene Glycol (PEG)

An immune response associated with IgM anti-PEG antibodies, manifested as symptoms of acute hypersensitivity and/or loss of drug effect, has occurred with JIVI administration [see Warnings and Precautions (5.1), Adverse Reactions (6.1) and Use in Specific Populations (8.4)]. In the clinical trials, the IgM anti-PEG antibodies disappeared within 4-6 weeks. No immunoglobulin class switching from IgM to IgG has been observed.

A low post-infusion Factor VIII level, in the absence of detectable Factor VIII inhibitors, may be due to loss of treatment effect related to high titers of anti-PEG IgM antibodies. In these cases, discontinue JIVI and switch patients to a different anti-hemophilic product.

A reduced recovery of Factor VIII after start of JIVI treatment may be due to transient low titers of anti-PEG IgM antibodies. In these cases, increase the dose of JIVI until recovery of Factor VIII returns to expected levels.

5.4 Monitoring Laboratory Tests

- If monitoring of Factor VIII activity is performed, use a validated chromogenic assay or a selected validated one-stage clotting assay [see Dosage and Administration (2.1)].
- Laboratories intending to measure the Factor VIII activity of JIVI should check their procedures for accuracy. For JIVI, select silica-based one-stage assays may underestimate the Factor VIII activity of JIVI in plasma samples; some reagents, e.g., with kaolin-based activators, have the potential for overestimation. Therefore, the suitability of the assay must be ascertained. If a validated one-stage clotting or chromogenic assay is not available locally, then use of a reference laboratory is recommended.
- Monitor for development of Factor VIII inhibitors. Perform a Bethesda inhibitor assay if expected Factor VIII plasma levels are not attained or if bleeding is not controlled with the expected dose of JIVI. Use Bethesda Units (BU) to report inhibitor titers.

6 ADVERSE REACTIONS

6.1 Clinical Trials Experience

Because clinical trials are conducted under widely varying conditions, adverse reaction rates observed in the clinical trials of a drug cannot be directly compared to rates in clinical trials of another drug and may not reflect the rates observed in clinical practice.

The safety database described in this section reflects the exposure of JIVI in four clinical studies, Study 1 (Safety and PK Study), Study 2 (PROTECT VIII), Study 3 (PROTECT Kids), and Study 4 (Alfa-PROTECT) [see Clinical Studies (14)]). A total of 256 patients received JIVI.

Patients who received JIVI for perioperative management (n=17) with treatment period of 2 to 3 weeks were excluded from pooled safety analysis but included in analysis for inhibitor development. The median exposure days (EDs) for adults, and pediatric patients ≥ 7 years of age was 92 EDs (range: 1–309) per patient.

Serious adverse reactions were reported in 5 patients (<2%), all were hypersensitivity reactions. Of the 5 patients, 1 patient was ≥ 7 years of age (see Anti-PEG Antibodies).

The most common adverse reactions (incidence ≥ 5%) were headache, fever, cough, and abdominal pain (see Table 3).

Table 3: Adverse Reactions reported in JIVI studies [Pooled data from Study 1, Study 2, Study 3, and Study 4.]
Adverse Reactions | All Patients 2-65 years of age n (%) n=256 | Patients ≥7 years of age n (%) n=208
Gastrointestinal Disorders
Abdominal pain | 12 (5%) | 10 (5%)
Nausea | 9 (4%) | 9 (4%)
Vomiting | 11 (4%) | 8 (4%)
General Disorders and Administration Site Conditions
Injection site reactions [Includes injection site pruritus, injection site rash, infusion site pain and vessel puncture site pruritus] | 7 (3%) | 6 (3%)
Fever | 23 (9%) | 13 (6%)
Immune System Disorders
Hypersensitivity | 9 (4%) | 4 (2%)
Nervous System Disorders
Dizziness | 3 (1%) | 3 (1%)
Dysgeusia | 1 (0.4%) | 0
Headache | 32 (13%) | 30 (14%)
Psychiatric Disorders
Insomnia | 5 (2%) | 5 (2%)
Respiratory, Thoracic and Mediastinal Disorders
Cough | 22 (9%) | 15 (7%)
Skin and Subcutaneous Tissue Disorders
Erythema [Includes erythema and erythema multiforme] | 3 (1%) | 2 (1%)
Pruritus | 2 (0.8%) | 1 (0.5%)
Rash [Includes rash and rash papular] | 10 (4%) | 5 (2%)
Vascular Disorders
Flushing | 1 (0.4%) | 1 (0.5%)

Immunogenicity: Anti-Drug Antibody-Associated Adverse Reactions

The observed incidence of anti-drug antibodies is highly dependent on the sensitivity and specificity of the assay. Differences in assay methods preclude meaningful comparisons of the incidence of anti-drug antibodies to JIVI in the studies described below with the incidence of anti-drug antibodies in studies with other products.

Immunogenicity was evaluated during clinical trials with JIVI in 158 (including surgery patients) previously treated adult and pediatric patients (≥ 12 years of age) severe hemophilia A (Factor VIII activity < 1%) patients with previous exposure to Factor VIII concentrates ≥ 150 EDs. There were 108 previously treated pediatric patients < 12 years of age [see Use in Specific Populations (8.4)].

Factor VIII Inhibitors

In Study 2, a Factor VIII inhibitor (1.7 BU/mL) was reported in 1 out of 144 patients [see Warning and Precautions (5.2)].

Anti-PEG Antibodies

In Study 2, immunogenicity against PEG was evaluated by anti-PEG screening and specific IgM anti-PEG ELISA assays. One patient (19 years of age) with asthma, presented at 4 exposure days (EDs) with a clinical hypersensitivity reaction after infusion of JIVI. The patient reported headache, abdominal pain, shortness of breath, and flushing, all of which resolved following his standard asthma treatment. No further medical intervention was required. The event was associated with a transient increase of IgM anti-PEG antibody titer, which was negative upon retest during follow-up within 30 days.

In Study 4 (7 to <12 years of age), one pediatric patient developed high titer neutralizing anti-PEG IgM antibodies (titer 1:64) after 2 EDs associated with low post-infusion FVIII levels and loss of efficacy. Antibodies disappeared after discontinuation and patient restarted treatment with JIVI 2 months later.

Three pediatric patients developed low titer and transient anti-PEG IgM antibodies (highest titer 1:4) within the first 4 EDs resulting in reduction of JIVI recovery (lowest recovery 0.8 kg/dl) in two patients and inconclusive data on recovery in one patient.

8 USE IN SPECIFIC POPULATIONS

8.1 Pregnancy

Risk Summary

There are no data with JIVI use in pregnant women to inform on drug-associated risk. Animal developmental and reproductive toxicity studies have not been conducted with JIVI. It is not known whether JIVI can cause fetal harm when administered to a pregnant woman or can affect reproduction capacity.

In the U.S. general population, the estimated background risk of major birth defects and miscarriage in clinically recognized pregnancies is 2–4% and 15–20%, respectively.

8.2 Lactation

Risk Summary

There is no information regarding the presence of JIVI in human milk, the effects on the breastfed infant, or the effects on milk production. The developmental and health benefits of breastfeeding should be considered along with the mother's clinical need for JIVI and any potential adverse effects on the breastfed infant from JIVI or from the underlying maternal condition.

8.4 Pediatric Use

The safety and effectiveness of JIVI have been established in previously treated pediatric patients 7 years of age and older. The use of JIVI in this age group was supported by evidence from three clinical studies, Study 2 (PROTECT VIII), Study 3 (PROTECT Kids) and Study 4 (Alfa-PROTECT), which included 108 pediatric patients 2 to <12 years of age and 12 pediatric patients 12 to <17 years of age [see Adverse Reactions (6), Clinical Pharmacology (12.3), and Clinical Studies (14)].

In Study 3 with 48 previously treated pediatric patients (PTPs) < 7 years of age, adverse reactions due to immune response to PEG were observed in 10 (21%) patients. In all 10 patients, loss of treatment effect due to neutralizing anti-PEG IgM antibodies was observed during the first 4 exposure days (EDs) and loss of treatment effect combined with hypersensitivity reactions was observed in 3 of those 10 patients (6%) [see Warnings and Precautions (5.3)]. Compared to adults and pediatric patients ≥12 years of age, a higher clearance, a shorter half-life and lower incremental recovery of Factor VIII have been observed in pediatric patients <12 years of age [see Clinical Pharmacology (12.3)].

In pediatric patients 2 to <7 years of age, efficacy of prophylaxis treatment with JIVI was demonstrated in 28 patients without an immune response to PEG and who had at least a 3 months treatment period. The median (interquartile range) ABR was 2.3 (1.2 – 5.2) and the mean (SD) ABR was 3.5 (3.4).

JIVI is not indicated for use in children below 7 years of age [see Clinical Studies (14)].

The safety and effectiveness of JIVI have not been studied in pediatric patients younger than 2 years of age.

8.5 Geriatric Use

JIVI has not been studied in patients 65 years of age and older.

11 DESCRIPTION

JIVI [antihemophilic factor (recombinant), PEGylated-aucl] is a sterile, nonpyrogenic, preservative-free, white to slightly yellow lyophilized powder for reconstitution with sterile Water for Injection (sWFI) as diluent for intravenous (IV) administration. The product is supplied in single-dose vials containing dosage strengths of 500, 1000, 2000 and 3000 IU in 2.5 mL fill size and 4000 IU in 5 mL fill size. For each dosage strength, the actual assayed potency is directly printed on each vial label. The container closure system consists of a 10 mL, Type I glass vial sealed with a bromobutyl grey stopper and an aluminum crimp seal with plastic flip-off cap plus vial adapter. The vial adapter was designed to connect with the sWFI, prefilled diluent syringe. The 500, 1000, 2000, and 3000 IU vials of JIVI are formulated with the following excipients: 59 mg glycine, 27 mg sucrose, 8.4 mg histidine, 4.7 mg sodium chloride, 0.7 mg calcium chloride, and 0.216 mg polysorbate 80. The 4000 IU vial of Jivi is formulated with the following quantities of these excipients: 114 mg glycine, 52 mg sucrose, 16.1 mg histidine, 9.1 mg sodium chloride, 1.9 mg calcium chloride, and 0.416 mg polysorbate 80. The pH of the reconstituted product is 6.6 to 7.0.

The specific activity of JIVI is approximately 10,000 IU/mg protein.

The active protein (or starting molecule), prior to conjugation is a recombinant B-domain deleted human coagulation Factor VIII (BDD-rFVIII) produced by recombinant DNA technology in Baby Hamster Kidney (BHK) cells.

JIVI is produced by site-specific conjugation of the BDD-rFVIII variant K1804C at the cysteine amino acid position 1804 (within the A3 domain) with a single maleimide-derivatized, 60 kilodalton (kDa) branched PEG (two 30 kDa PEG) moiety. The A3 domain was selected for conjugation to provide both a consistent coagulation activity and high PEGylation efficiency.

The molecular weight of JIVI is approximately 234 kDa based on the calculated average molecular weight of the BDD-rFVIII variant of 165 kDa, plus glycosylation (~4 kDa), and the average molecular weight of the PEG-maleimide of approximately 60 kDa. Functional characterization of JIVI shows comparable mechanism of action to that of rFVIII product with an extended plasma half-life [see Clinical Pharmacology (12.1)].

The manufacturing process of JIVI involves propagation of the recombinant production cell line with the harvest isolation process consisting of continuous filtration of tissue culture fluid and anion exchange chromatography on a membrane adsorber capsule. The process intermediate is purified from process- and product-related impurities using a series of chromatography and filtration steps, including 20 nm viral filtration, prior to conjugation to the 60 kDa maleimide PEG moiety. The mono-PEGylated JIVI active molecule is separated from product-related species by chromatography and then formulated by ultrafiltration. The cell culture, PEGylation, purification process and formulation used in the manufacture of JIVI do not use any additives of human or animal origins.

12 CLINICAL PHARMACOLOGY

12.1 Mechanism of Action

JIVI, a site-specifically PEGylated recombinant antihemophilic factor [see Description (11)], temporarily replaces the missing coagulation Factor VIII. The site-specific PEGylation in the A3 domain reduces binding to the physiological Factor VIII clearance receptors resulting in an extended half-life and increased AUC [see Clinical Pharmacology (12.3)].

12.2 Pharmacodynamics

The aPTT is prolonged in people with hemophilia A.

Determination of aPTT is a conventional in vitro assay for biological activity of Factor VIII. Treatment with JIVI normalizes the aPTT similar to that achieved with plasma-derived Factor VIII. The administration of JIVI increases plasma levels of Factor VIII and can temporarily correct the coagulation defect in hemophilia A patients.

12.3 Pharmacokinetics

The PK of JIVI was evaluated in two cohorts after single doses of 25 IU/kg and 60 IU/kg and after 25 IU/kg given twice weekly and 60 IU/kg given once weekly for 8 weeks in Study 1 (Safety and PK study).

The PK profile obtained at Week 8, after repeated dosing, was comparable with the PK profile obtained after the first dose.

In Study 2 (PROTECT VIII), the PK of JIVI was investigated in 22 previously treated severe Hemophilia A patients (≥ 12 years of age) following administration of a single dose, 60 IU/kg, of JIVI prior to initiation of prophylactic treatment and in 16 patients after 6 months of prophylaxis treatment with JIVI. In Study 3 (PROTECT Kids) the PK of JIVI was investigated in 12 previously treated severe Hemophilia A patients (7 to <12 years of age) following administration of a single dose, 60 IU/kg, of JIVI. Table 4 summarizes the PK parameters of adults and adolescents (≥12 years of age) and children (7 to <12 years of age) after a single dose of JIVI. Higher clearance, a shorter half-life and lower incremental recovery of JIVI have been observed in children 7 to <12 years of age.

Table 4: Pharmacokinetic Parameters (Arithmetic Mean ± SD) for JIVI following a Single Dose based on Chromogenic and One-stage assay
PK Parameters (unit) | Adults and Adolescents (≥ 12 years of age) |  |  |  | Children (7 to <12 years of age)
PK Parameters (unit) | Chromogenic assay |  | One-stage assay |  | Chromogenic assay
PK Parameters (unit) | 25 IU/kg | 60 IU/kg [Combined data from Study 1 and Study 2] | 25 IU/kg | 60 IU/kg | 60 IU/kg
PK Parameters (unit) | n=7 | n=29 | n=7 | n=29 | n=12
AUC (IU*h/dL) | 1640 ± 550 | 4060 ± 1420 | 1640 ± 660 | 4150 ± 1060 | 2890± 547
Cmax (IU/dL) | 64.2 ± 9.2 | 167 ± 30 | 69.4 ± 11.3 | 213 ± 71 | 130 ± 25.0 [n=13]
t½ (h) | 18.6 ± 4.6 | 17.9 ± 4.0 | 21.4 ± 13.1 | 17.4 ± 3.8 | 16.0± 3.61 [n=14]
MRTIV (h) | 26.7 ± 6.6 | 25.8 ± 5.9 | 29.0 ± 14.0 | 24.5 ± 5.4 | 24.1± 5.97
Vss (mL/kg) | 42.8 ± 5.0 | 39.4 ± 6.3 | 44.7 ± 5.4 | 36.0 ± 6.5 | 50.5± 9.89
CL (mL/h/kg) | 1.68 ± 0.39 | 1.63 ± 0.52 | 1.74 ± 0.54 | 1.52 ± 0.38 | 2.14± 0.433
Recovery [(IU/dL)/(IU/kg)] | 2.13 ± 0.47 | 2.53 ± 0.43 [Recovery value could not be calculated for one patient] | 2.21 ± 0.55 | 3.25 ± 0.84b | 1.93 ± 0.54 [Data obtained from all patients' recovery samples, excluding those with anti-drug antibodies, on a twice weekly regimen (n=42) with a range of 1.1-3.8 kg/dL]
AUC: area under the curve; Cmax: maximum drug concentration in plasma after single dose; t½: terminal half-life; MRTIV: mean residence time after an IV administration; VSS: apparent volume distribution at steady-state; CL: clearance

13 NONCLINICAL TOXICOLOGY

13.1 Carcinogenesis, Mutagenesis, Impairment of Fertility

Studies in animals to evaluate the carcinogenic or genotoxic potential of JIVI, or studies to determine the effects of JIVI on fertility, have not been performed. No effect on male and female reproductive organs was seen in repeated-administration toxicity studies. Genotoxicity studies conducted with the PEG component of JIVI showed no indication of genotoxicity.

13.2 Animal Toxicology and/or Pharmacology

No adverse effects were observed in immune-deficient rats intravenously injected with JIVI (40–1200 IU/kg/injection), twice weekly for 26 weeks. No evidence of accumulation of the PEG component of JIVI was detected by immunohistochemical staining in the brain (including the choroid plexus), spleen, or kidneys in animals sacrificed at 13 and 26 weeks.

14 CLINICAL STUDIES

The efficacy of JIVI for on-demand treatment, perioperative management of bleeding, and routine prophylaxis was evaluated in three clinical studies, Study 2 (PROTECT VIII; NCT01580293) in patients ≥12 years, Study 3 (PROTECT Kids; NCT01775618) in patients 2 to < 12 years of age, and Study 4 (Alfa-PROTECT; NCT05147662) in patients 7 to <12 years of age as described below.

Immunocompetent patients with severe hemophilia A (Factor VIII activity <1%) and no history of Factor VIII inhibitors were eligible for the trials.

Study 2

A multinational, prospective, single-arm study in adult and pediatric previously treated patients (PTP) 12 to 65 years of age with ≥ 150 exposure days (EDs). The study consisted of three parts: Part A (Weeks 0 – 36); an optional extension phase for patients who completed Part A to accumulate at least 100 EDs; and Part B, a surgical phase.

Part A of the study evaluated the PK (single dose of 60 IU/kg), safety and efficacy of JIVI for on-demand treatment and routine prophylaxis. A total of 134 PTPs received at least one infusion of JIVI, including 20 on-demand treating patients with a median age of 48 years (range: 22 to 61), 114 prophylaxis-treating patients with a median age of 33 years (range: 12 to 62). The prophylaxis group (n=112, excluding 2 patients who dropped out after single infusion) completed a 10-week run-in phase during which patients received 25 IU/kg twice weekly JIVI before patients were randomized to the different dosing regimens based on their bleeding frequency for weeks 10–36. The on-demand group (n=20) treated with JIVI on-demand for the full 36 weeks. One hundred thirty two patients were evaluable for efficacy, of which 126 (94%) patients (prophylaxis group: n=108; on-demand group: n=18) completed the 36 weeks of treatment in Part A. The primary efficacy endpoint was annualized bleed rate (ABR).

A total of 121 patients received treatment during the extension phase (107 patients received prophylaxis and 14 patients continued on-demand treatment).

Safety and efficacy of JIVI in hemostasis during major surgical procedures were evaluated in 17 patients in Part B.

Study 3

A multi-center, prospective, single-arm trial to evaluate the pharmacokinetics, safety, and efficacy of JIVI for prophylaxis and treatment of bleeding in previously treated pediatric patients <12 years of age with severe hemophilia A. The study consisted of three parts: the main study with 2 subgroups by age (<6 years and 6 to <12 years), an expansion study in children <6 years and an optional extension study. The main study evaluated the PK (single dose of 60 IU/kg) in each age subgroup, safety and efficacy of JIVI for on-demand treatment and routine prophylaxis for a minimum of 50 EDs and 6 months. A total of 73 PTPs were included, and were treated prophylactically with regimens of twice weekly (25-60 IU/kg) or every 5 days (45-60 IU/kg) or every 7 days at any given time as per investigator's discretion. The median age was 5 years (range: 2 to 11). The primary efficacy endpoint was the annualized bleed rate (ABR).

Study 4

A multi-center, prospective, single-arm, study to evaluate the safety of JIVI infusions for prophylaxis and treatment of bleeding in previously treated pediatric patients 7 to <12 years of age with severe hemophilia A. The study evaluated the potential risk of hypersensitivity and loss of drug effect associated with an immune response to polyethylene glycol (PEG) during the first 4 exposure days to JIVI. A total of 35 patients with a median age of 8 years (range: 7 to 11) were enrolled and treated prophylactically for a minimum of 50 EDs and 26 weeks. The patients received a treatment regimen of JIVI twice weekly (40-60 IU/kg) at investigator's discretion. Thirty-two patients completed the treatment phase and were offered continuation in an 18 months extension study. A key secondary endpoint was the annualized bleed rate (ABR).

On-demand Treatment and Control of Bleeding Episodes

In Study 2, approximately 91% of bleeds were successfully treated with 1 or 2 infusions in both the on-demand and prophylaxis groups. In Studies 3 and 4, approximately 97% of bleeds were successfully treated with 1 or 2 infusions. Efficacy in control of bleeding episodes is summarized in Table 5.

Table 5: On-Demand Treatment and Control of Bleeding Episodes
Characteristics of Bleeding Episodes | Adults and Adolescents (≥12 Years of Age) |  | Children (7 to <12 Years of Age) [Pooled patients from Studies 3 and 4 in the age group 7 to <12 years of age with a twice weekly regimen and at least a 3 months treatment period, modified ITT set]
Characteristics of Bleeding Episodes | On-Demand n=20 | Routine Prophylaxis n=112 | Routine prophylaxis n=42
Total number of bleeds treated | 388 [For two bleeds in the on-demand group and one bleed in the prophylaxis group, limited information is available.] | 317a | 36
1 infusion | 309 (80%) | 263 (83%) | 30 (83%)
2 infusions | 45 (11%) | 22 (7%) | 5 (14%)
≥ 3 infusions | 34 (9%) | 32 (10%) | 1 (3%)
Number of bleeds with assessment | 384 | 310 | 36
Number of responses to treatment of bleeds assessed as 'Excellent' or 'Good' (%) | 253 (66%) | 256 (83%) | 30 (83%)
Number of responses to treatment of bleeds assessed as 'Moderate' | 115 (30%) | 47 (15%) | 5 (14%)
Number of responses to treatment of bleeds assessed as 'Poor' | 16 (4%) | 7 (2%) | 1 (3%)
Definitions:
Excellent: Abrupt pain relief and/or improvement in signs of bleeding with no additional infusion administered
Good: Definite pain relief and/or improvement in signs of bleeding, but possibly requiring more than one infusion for complete resolution
Moderate: Probable or slight improvement, with at least one additional infusion for complete resolution
Poor: No improvement or condition worsened

Perioperative Management

In Study 2, a total of 17 patients successfully completed 20 major surgeries. In Part B of the study, 14 patients underwent 17 surgeries and in the extension study, 3 patients underwent 3 surgeries, using JIVI for hemostasis. There were 6 non-orthopedic surgeries and 14 orthopedic surgeries (3 arthroplasties, 6 joint replacements, 3 synovectomies, and 2 other joint procedures). Treatment with JIVI provided 'good' or 'excellent' hemostatic control during all 20 major surgeries. The initial JIVI pre-surgery doses administered ranged between 2500 and 5000 IU. The median total dose per surgery was 219 IU/kg with a median of 35 IU/kg/infusion and a median of 7 infusions per surgery (up to 3 weeks). The median number of infusions on day of surgery was 2 (range: 1 – 3).

An additional 17 minor surgeries were performed in 10 patients during Part A of Study 2 . The adequacy of hemostasis during minor surgeries was assessed as either 'good' or 'excellent' in 16 cases and not reported in one case.

A total of 7 patients in the age group 7 to <12 years, 5 patients in Study 3 and 2 patients in Study 4 had 10 minor surgeries. The adequacy of hemostasis during minor surgeries was assessed as either 'good' or 'excellent' in 4 cases, moderate in 1 case and not reported in 5 cases.

Routine Prophylaxis

Adults and Adolescents (≥12 years of age)

In Study 2, the primary assessment of efficacy was based on 110 patients who received JIVI for routine prophylaxis during Weeks 10–36 of Part A. Of these, 107 patients participated in the optional extension phase.

All patients in the prophylaxis treatment arms began treatment with twice weekly infusions of 25 IU/kg for 10 weeks (run-in phase). After the run-in phase (Weeks 0 – 10), patients (97 of 110; 88%) who experienced ≤ 1 breakthrough bleeds during the first 10 weeks of treatment qualified for randomization to a less frequent dosing regimen, 86 were randomized 1:1 (n = 43 to either arm) to either every 5 days of 45–60 IU/kg, with a median of 45.3 IU/kg (range: 39 to 58) or every 7 days for an additional 26 weeks (Weeks 10–36; 6.5 months). Eleven additional patients, who completed the run-in phase and were eligible for randomization after the every 5- and 7-day arms were filled, remained in the twice weekly regimen of 30–40 IU/kg, with a median of 30.6 (range: 29 to 41). Dose adjustments were recommended for randomized patients who experienced 2 joint and/or muscle bleeds within a 10-week interval during week 10–36 and included the increase of the dose up to 60 IU/kg or changing to more frequent dosing.

Twelve percent of patients (n=13) who experienced ≥ 2 spontaneous bleeds during the 10 week run-in phase were ineligible for randomization and continued on the 2 times per week dosing frequency at a higher dose of 30–40 IU/kg, with a median of 39.2 IU/kg (range: 33 to 42) for the additional 26 weeks. Nine of the 13 patients were on prior prophylaxis (n=9) and were observed to have a higher mean number of bleeds in the 12 months prior to study entry of 17.4 compared to a mean of 5–7 bleeds for all other patients eligible for randomization to less frequent dosing regimens. The median cumulative number of days in the study (Part A plus extension) was 716 (range: 0 to 952) with a median number of 137 EDs (range: 1 to 309).

In Weeks 10–36 of Part A, the majority [99/110 (90%)] of patients did not change their treatment regimens. All patients randomized to the every 5-day regimen (43/43 patients) or assigned to the 2 times per week regimen (24/24 patients) remained in their assigned treatment arm until Week 36. Treatment success in the every 7 day arm was not established. For ABR by regimen, see Table 6.

During the extension phase of Study 2, the median prophylaxis dose was maintained for the median duration of 1.3 years (range: 0.1–1.9).

An analysis compared ABRs between the on-demand group and the different prophylaxis regimens indicated that the ABR was significantly reduced by 88.2% in the every 5-days (p<0.0001) in comparison with on-demand treatment. There was no significant difference in ABRs between the twice weekly and extended interval treatment arms. Nineteen (19) of 43 patients in the every 5-day arm (44%) experienced no bleeding episode during week 10–36.

Table 6: ABR [The ABR was calculated based on the time treated in the assigned treatment regimen.] for Treated Bleeds by Treatment Regimen in ITT population of Adults and Adolescents (≥12 Years of Age)
Main Study (Week 10 – 36)
Treatment Regimen (n) |  |  | Type of Bleed |  |  | Patients with Zero Bleeds, % (n)
Treatment Regimen (n) |  |  | Total | Spontaneous | Joint | Patients with Zero Bleeds, % (n)
2 times per week 30–40 IU/kg | Eligible for randomization (11) | Median (Q1; Q3) | 1.9 (0.0; 5.2) | 0.0 (0.0; 1.9) | 1.9 (0.0; 5.2) | 46% (5)
2 times per week 30–40 IU/kg | Eligible for randomization (11) | Mean (SD) | 2.2 (2.7) | 1.2 (2.2) | 2.2 (2.7) | 46% (5)
2 times per week 30–40 IU/kg | Ineligible for randomization (13) | Median (Q1; Q3) | 4.1 (2.0; 10.6) | 3.9 (0.0; 4.1) | 4.0 (2; 8.0) | 15% (2)
2 times per week 30–40 IU/kg | Ineligible for randomization (13) | Mean (SD) | 7.2 (7.5) | 3.9 (4.3) | 5.2 (4.8) | 15% (2)
Every 5 days 45 – 60 IU/kg (43) |  | Median (Q1; Q3) | 1.9 (0.0; 4.2) | 0.0 (0.0; 4) | 1.9 (0.0; 4) | 44% (19)
Every 5 days 45 – 60 IU/kg (43) |  | Mean (SD) | 3.3 (4.3) | 1.8 (2.6) | 2.5 (3.5) | 44% (19)
On-Demand [The treatment period for on-demand was Weeks 0 – 36.] (20) |  | Median (Q1; Q3) | 24.1 (17.8; 37.3) | 14.3 (7.3; 22.7) | 16.3 (11.6; 30.3) | 0 (0)
On-Demand [The treatment period for on-demand was Weeks 0 – 36.] (20) |  | Mean (SD) | 28.8 (17.8) | 17.2 (13.2) | 22.2 (16.7) | 0 (0)

Children (7 to <12 years of age)

In Study 3 and Study 4, the efficacy of prophylactic treatment was assessed in 57 patients. Forty-two of 57 patients were treated with a twice weekly regimen of 25-60 IU/kg, with a median dose per infusion of 51.7 IU/kg (range: 22 to 69). The median cumulative number of days in the study for patients in the twice weekly treatment group was 182 (range: 172-238 days) with a median number of 53.5 EDs (range: 35-62 EDs). The ABR is presented in Table 7.

Table 7: ABR for Treated Bleeds in mITT [Modified ITT population included patients with at least a 3 months treatment period] population of Children (7 to <12 Years of Age)
Treatment Regimen (n) [Pooled patients from Study 3 and Study 4 in the age group 7 to <12 years of age, modified ITT set] |  | Type of Bleed |  |  | Patients with Zero Bleeds, % (n)
Treatment Regimen (n) [Pooled patients from Study 3 and Study 4 in the age group 7 to <12 years of age, modified ITT set] |  | Total | Spontaneous | Joint | Patients with Zero Bleeds, % (n)
2 times per week 25-60 IU/kg (n=42) | Median (Q1; Q3) | 0.0 (0.0; 2.0) | 0.0 (0.0; 0.0) | 0.0 (0.0; 0.0) | 67% (28)
2 times per week 25-60 IU/kg (n=42) | Mean (SD) | 1.7 (3.0) | 0.9 (2.0) | 0.9 (2.1) | 67% (28)

16 HOW SUPPLIED/STORAGE AND HANDLING

How Supplied

JIVI is available as a lyophilized powder in single-dose glass vials, one vial per carton. It is supplied with a sterile vial adapter with 15-micrometer filter and a prefilled diluent glass barrel syringe, which together serve as a needleless reconstitution system. The prefilled diluent syringe contains sterile Water for Injection, USP. An administration set is also provided in the package. Available sizes:

Nominal Strength (IU) | Diluent (mL) | Kit NDC Number | Color Code
500 | 2.5 | 0026-3942-25 | Green
1000 | 2.5 | 0026-3944-25 | Red
2000 | 2.5 | 0026-3946-25 | Yellow
3000 | 2.5 | 0026-3948-25 | Gray
4000 | 5 | 0026-3950-50 | Purple

Actual Factor VIII activity in IU is stated on the label of each JIVI vial.

The product vial and diluent syringe are not made with natural rubber latex.

Storage and Handling

Product as Packaged for Sale

- Store JIVI at +2°C to +8°C (36°F to 46°F) for up to 24 months from the date of manufacture. Do not freeze. Within this period, JIVI may be stored for a single period of up to 6 months at temperatures up to +25°C or 77°F.
- Record the starting date of room temperature storage on the unopened product carton. Once stored at room temperature, do not return the product to the refrigerator. The shelf-life then expires after storage at room temperature for 6 months, or after the expiration date on the product vial, whichever is earlier.
- Do not use JIVI after the expiration date indicated on the vial.
- Protect JIVI from extreme exposure to light and store the vial with the lyophilized powder in the carton prior to use.

Product After Reconstitution

- Administer reconstituted JIVI as soon as possible. If you do not administer the reconstituted JIVI immediately, then store at room temperature for no longer than 3 hours.
- Do not use JIVI if the reconstituted solution is cloudy or has particulate matter.
- Use the administration set provided.

17 PATIENT COUNSELING INFORMATION

- Advise the patient to read the FDA-approved patient labeling (Patient Information and Instructions for Use).
- Hypersensitivity reactions are possible with JIVI [see Warnings and Precautions (5.1)]. Warn patients of the early signs of hypersensitivity reactions (including tightness of the chest or throat, dizziness, mild hypotension and nausea during infusion) which can progress to anaphylaxis. Advise patients to discontinue use of the product if these symptoms occur and seek immediate emergency treatment with resuscitative measures such as the administration of epinephrine and oxygen.
- Inhibitor formation may occur at any time in the treatment of a patient with hemophilia A [see Warnings and Precautions (5.2)]. Advise patients to contact their physician or treatment center for further treatment and/or assessment, if they experience a lack of clinical response to Factor VIII replacement therapy, as this may be a manifestation of an inhibitor.
- Allergic reactions to polyethylene glycol (PEG), a component of JIVI, are possible. Advise patients to contact their physician or treatment center if they experience a lack of clinical response from their usual dose. [see Warnings and Precautions (5.3) and Adverse Reactions (6.1)]
- Advise patients to discard all equipment, including any unused product, in an appropriate container.
- Advise patients to consult with their healthcare provider prior to travel. Advise patients to bring an adequate supply of JIVI while traveling based on their current regimen of treatment.

Bayer HealthCare LLC
Whippany, NJ 07981 USA
U.S. License No. 0008

PATIENT INFORMATION
JIVI (JIHV-ee)
[antihemophilic factor (recombinant), PEGylated-aucl]

This leaflet summarizes important information about JIVI with vial adapter. Please read it carefully before using this medicine. This information does not take the place of talking with your healthcare provider, and it does not include all of the important information about JIVI. If you have any questions after reading this, ask your healthcare provider.
Do not attempt to self-infuse, unless your healthcare provider or hemophilia center has taught you how to self-infuse.

What is JIVI?
JIVI is an injectable medicine used to replace clotting factor (Factor VIII or antihemophilic factor) that is missing in people with hemophilia A (congenital Factor VIII deficiency).
JIVI is used to treat and control bleeding in previously treated adults and children 7 years of age and older with hemophilia A. Your healthcare provider may also give you JIVI when you have surgery. JIVI can reduce the number of bleeding episodes in adults and children 7 years of age and older with hemophilia A when used regularly (prophylaxis).
JIVI is not for use in children < 7 years of age or in previously untreated patients.
JIVI is not used to treat von Willebrand disease.

Who should not use JIVI?
You should not use JIVI if you:

- Are allergic to rodents (like mice and hamsters).
- Are allergic to any ingredients in JIVI.

What should I tell my healthcare provider before I use JIVI?
Tell your healthcare provider about:

- All of your medical conditions that you have or had.
- All of the medicines you take, including all prescription and non-prescription medicines, such as over-the-counter medicines, supplements, or herbal remedies.
- Pregnancy or planning to become pregnant. It is not known if JIVI may harm your unborn baby.
- Breastfeeding. It is not known if JIVI passes into the milk.
- Whether you have been told that you have inhibitors to Factor VIII.

What are the possible side effects of JIVI?
The common side effects of JIVI are headache, fever, cough, and abdominal pain.
Allergic reactions may occur with JIVI. Call your healthcare provider right away and stop treatment if you get tightness of the chest or throat, dizziness, decrease in blood pressure, or nausea. Allergic reactions to polyethylene glycol (PEG), a component of JIVI, are possible.
Your body can also make antibodies, called "inhibitors", against JIVI, or certain components of JIVI, such as polyethylene glycol (PEG), which may stop JIVI from working properly. Consult with your healthcare provider to make sure you are carefully monitored with blood tests for the development of inhibitors to Factor VIII.
If your bleeding is not being controlled with your usual dose of JIVI, consult your doctor immediately. You may have developed Factor VIII inhibitors or antibodies to PEG and your doctor may carry out tests to confirm this.
These are not all the possible side effects with JIVI. You can ask your healthcare provider for information that is written for healthcare professionals.
Tell your healthcare provider about any side effect that bothers you or that does not go away.

What are the JIVI dosage strengths?
JIVI with 2.5 mL or 5mL sterile Water for Injection (sWFI) comes in five different dosage strengths labeled as International Units (IU): 500 IU, 1000 IU, 2000 IU, 3000 IU, and 4000 IU. The five different strengths are color-coded as follows:

Green

500 IU with 2.5 mL sWFI

Red

1000 IU with 2.5 mL sWFI

Yellow

2000 IU with 2.5 mL sWFI

Gray

3000 IU with 2.5 mL sWFI

Purple

4000 IU with 5 mL sWFI

How do I store JIVI ?
Do not freeze JIVI .
Store JIVI at +2°C to +8°C (36°F to 46°F) for up to 24 months from the date of manufacture. Within this period, JIVI may be stored for a period of up to 6 months at temperatures up to +25°C or 77°F.
Record the starting date of room temperature storage clearly on the unopened product carton. Once stored at room temperature, do not return the product to the refrigerator. The product then expires after storage at room temperature for 6 months, or after the expiration date on the product vial, whichever is earlier. Store vials in their original carton and protect them from extreme exposure to light.
Administer reconstituted JIVI as soon as possible. If not, store at room temperature for no longer than 3 hours.
Throw away any unused JIVI after the expiration date.
Do not use reconstituted JIVI if it is not clear.

What else should I know about JIVI and hemophilia A?
Medicines are sometimes prescribed for purposes other than those listed here. Do not use JIVI for a condition for which it is not prescribed. Do not share JIVI with other people, even if they have the same symptoms that you have.
This leaflet summarizes the most important information about JIVI that was written for healthcare professionals.
Bayer HealthCare LLC
Whippany, NJ 07981 USA
U.S. License No. 0008

This Patient Information has been approved by the U.S. Food and Drug Administration.

Revised: 5/2025

INSTRUCTIONS FOR USE

JIVI

[antihemophilic factor (recombinant), PEGylated-aucl]

Do not attempt to self-infuse unless you have been taught how by your healthcare provider or hemophilia center.

You should always follow the specific instructions given by your healthcare provider. The steps listed below are general guidelines for using JIVI. If you are unsure of the procedures, please call your healthcare provider before using.

If bleeding is not controlled after using JIVI, then call your healthcare provider right away.

Your healthcare provider will prescribe the dose that you should take.

Your healthcare provider may need to take blood tests from time to time.

Talk to your healthcare provider before traveling. You should plan to bring enough JIVI for your treatment during this time.

See the step-by-step instructions below for reconstituting (mixing) JIVI with vial adapter. Follow the specific infusion instruction leaflet included with the infusion set provided.

Carefully handle JIVI. Dispose of all materials, including any leftover reconstituted JIVI product, in an appropriate container.

Use only the components for reconstitution and administration that are provided with each package of JIVI. If a package is opened or damaged, do not use this component. If these components cannot be used, please contact your healthcare provider. Gather all the materials needed for the infusion.

Reconstitution

Always work on a clean flat surface and wash your hands before performing the following procedures.

1. Warm the unopened diluent syringe and the concentrate vial to a temperature not to exceed 37°C or 99°F.

2. Remove protective cap from the vial (A). Aseptically cleanse the rubber stopper with a sterile alcohol swab, being careful not to handle the rubber stopper.

3. Place product vial on a firm, non-skid surface. Peel off the paper cover on the vial adapter plastic housing. Do not remove the adapter from the plastic housing. Holding the adapter housing, place over the product vial and firmly press down (B). The adapter will snap over the vial cap. Do not remove the adapter housing at this step.

4. Holding the syringe by the barrel, snap the syringe cap off the tip (C). Do not touch the syringe tip with your hand or any surface. Set the syringe aside for further use.

5. Now remove and discard the adapter plastic housing (D).

6. Attach the prefilled syringe to the vial adapter thread by turning clockwise (E).

7. Remove the clear plastic plunger rod from the carton. Grasp the plunger rod by the top plate. Avoid touching the sides and threads of the plunger rod. Attach the plunger rod by turning it clockwise into the threaded rubber stopper of the prefilled syringe (F).

8. Inject the diluent slowly by pushing down on the plunger rod (G).

9. Swirl vial gently until all powder on all sides of the vial is dissolved (H). Do not shake vial. Be sure that all powder is completely dissolved. Do not use if solution contains visible particles or is cloudy.

10. Push down on the plunger to push all air back into the vial. Then while holding the plunger down, turn the vial with syringe upside-down (invert) so the vial is now above the syringe (I). Pooling: Pooling is a process of combining the contents of multiple vials into a syringe. If the dose requires more than one vial, reconstitute each vial as described above with the diluent syringe provided. To combine the contents of the vials, use a larger plastic syringe (not provided) to pool the solution into the syringe and administer as usual.

11. Filter the reconstituted product to remove potential particulate matter in the solution. Filtering is achieved by using the vial adapter. Withdraw all the solution through the vial adapter into the syringe by pulling the plunger rod back slowly and smoothly (J). Tilt the vial to the side and back to make sure all the solution has been drawn toward the large opening in the rubber stopper and into the syringe. Remove as much air as possible before removing the syringe from the vial by slowly and carefully pushing the air back into the vial.

12. Detach the syringe with plunger rod from the vial adapter by turning counter-clockwise. Attach the syringe to the infusion set provided and inject the reconstituted product intravenously (K). NOTE: follow instructions for infusion set provided.

Rate of Administration

The entire dose of JIVI can usually be infused within 1 to 15 minutes. The maximum rate is 2.5 mL per minute. Your healthcare provider will determine the rate of administration that is best for you.

Resources at Bayer available to the patient:

For Adverse Reaction Reporting, contact Bayer Medical Communications 1-888-84-BAYER (1-888-842-2937)

To receive more product information, contact JIVI Customer Service 1-888-606-3780

Bayer Reimbursement HELPline 1-800-288-8374

For more information, visit http://www.jivi-us.com

Bayer HealthCare LLC
Whippany, NJ 07981 USA

U.S. License No. 0008

This Instructions for Use has been approved by the U.S. Food and Drug Administration.
Revised: 5/2025

PACKAGE/LABEL PRINCIPAL DISPLAY PANEL

NDC 0026-3942-25

Jivi

500 IU Range

Antihemophilic Factor (Recombinant)

PEGylated-aucl

Recombinant Factor VIII

with Vial Adapter

For Intravenous Use Only

Needleless Reconstitution Set

PACKAGE/LABEL PRINCIPAL DISPLAY PANEL

NDC 0026-3944-25

Jivi

1000 IU Range

Antihemophilic Factor (Recombinant)

PEGylated-aucl

Recombinant Factor VIII

with Vial Adapter

For Intravenous Use Only

Needleless Reconstitution Set

PACKAGE/LABEL PRINCIPAL DISPLAY PANEL

NDC 0026-3946-25

Jivi

2000 IU Range

Antihemophilic Factor (Recombinant)

PEGylated-aucl

Recombinant Factor VIII

with Vial Adapter

For Intravenous Use Only

Needleless Reconstitution Set

PACKAGE/LABEL PRINCIPAL DISPLAY PANEL

NDC 0026-3948-25

Jivi

3000 IU Range

Antihemophilic Factor (Recombinant)

PEGylated-aucl

Recombinant Factor VIII

with Vial Adapter

For Intravenous Use Only

Needleless Reconstitution Set

PACKAGE/LABEL PRINCIPAL DISPLAY PANEL

NDC 0026-3950-50

Jivi

4000 IU Range

Antihemophilic Factor (Recombinant)

PEGylated-aucl

Recombinant Factor VIII

with Vial Adapter

For Intravenous Use Only

Needleless Reconstitution Set